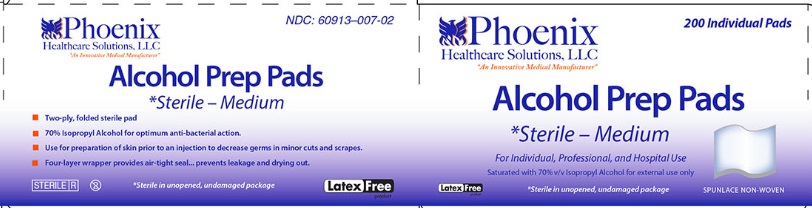 DRUG LABEL: Alcohol Prep Pads
NDC: 60913-007 | Form: SWAB
Manufacturer: PHOENIX HEALTHCARE SOLUTIONS, LLC
Category: otc | Type: HUMAN OTC DRUG LABEL
Date: 20251023

ACTIVE INGREDIENTS: ISOPROPYL ALCOHOL 70 mL/100 mL
INACTIVE INGREDIENTS: WATER

Phoenix Alcohol Prep Pads

Active Ingredients

Isopropyl alcohol 70% v/v

Purpose

Antiseptic

Use:

For preparation of the skin prior to injection; to decrease germs in minor cuts and scrapes.

Warnings:

- For external use only. Flammable; keep away from fire and flame

Keep out of reach of children.

If swallowed, get medical help or contact a Poison Control Center immediately.

Caution:

Do not apply to irritated skin.

Do not use

in the eyes, or on mucous membranes. In case of deep or puncture wounds, consult a doctor.

Directions:

Wipe injection site vigorously.

Other information:

Store at room temperature

Inactive ingredients:

Water

Principal Display Panel

Phoenix Healthcare Solutions,LLC

An Innovative Medical Manufacturer

NDC 60913-007-02

200 Individual Pads

Alcohol Prep Pads

Sterile Medium

For Individual, Professional and Hospital Use

Saturated with 70% v/v Isopropyl Alcohol for external use only

Latex Free

Sterile in unopened, undamaged package

Spunlace non-woven